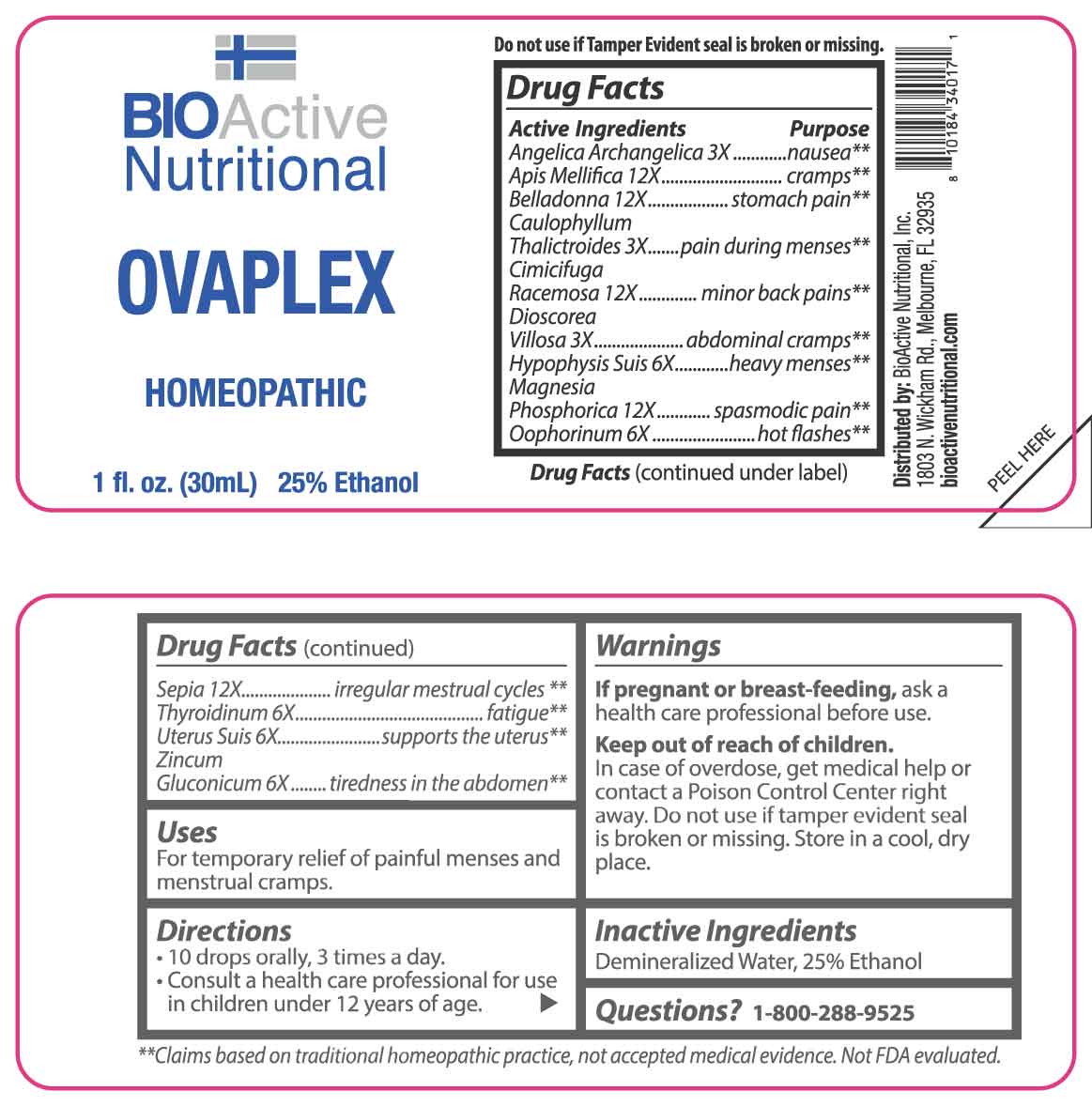 DRUG LABEL: Ovaplex
NDC: 43857-0204 | Form: LIQUID
Manufacturer: BioActive Nutritional, Inc.
Category: homeopathic | Type: HUMAN OTC DRUG LABEL
Date: 20250402

ACTIVE INGREDIENTS: ANGELICA ARCHANGELICA ROOT 3 [hp_X]/1 mL; CAULOPHYLLUM THALICTROIDES ROOT 3 [hp_X]/1 mL; DIOSCOREA VILLOSA TUBER 3 [hp_X]/1 mL; SUS SCROFA OVARY 6 [hp_X]/1 mL; SUS SCROFA PITUITARY GLAND 6 [hp_X]/1 mL; THYROID 6 [hp_X]/1 mL; SUS SCROFA UTERUS 6 [hp_X]/1 mL; ZINC GLUCONATE 6 [hp_X]/1 mL; APIS MELLIFERA 12 [hp_X]/1 mL; ATROPA BELLADONNA 12 [hp_X]/1 mL; BLACK COHOSH 12 [hp_X]/1 mL; MAGNESIUM PHOSPHATE, DIBASIC TRIHYDRATE 12 [hp_X]/1 mL; SEPIA OFFICINALIS JUICE 12 [hp_X]/1 mL
INACTIVE INGREDIENTS: WATER; ALCOHOL

DRUG FACTS:

ACTIVE INGREDIENTS:

Angelica Archangelica 3X, Apis Mellifica 12X, Belladonna 12X, Caulophyllum Thalictroides 3X, Cimicifuga Racemosa 12X, Dioscorea Villosa 3X, Hypophysis Suis 6X, Magnesia Phosphorica 12X, Oophorinum 6X, Sepia 12X, Thyroidinum 6X, Uterus Suis 6X, Zincum Gluconicum 6X.

PURPOSE:

Angelica Archangelica - nausea,** Apis Mellifica - cramps,** Belladonna – stomach pain,** Caulophyllum Thalictroides – pain during menses,** Cimicifuga Racemosa – minor back pains,** Dioscorea Villosa – abdominal cramps,** Hypophysis Suis – heavy menses,** Magnesia Phosphorica – spasmodic pain,** Oophorinum – hot flashes,** Sepia – irregular menstrual cycles,** Thyroidinum - fatigue,** Uterus Suis – supports the uterus,** Zincum Gluconicum – tiredness in the abdomen**
**Claims based on traditional homeopathic practice, not accepted medical evidence. Not FDA Evaluated.

USES:

For temporary relief of painful menses and menstrual cramps.

WARNINGS:

If pregnant or breast-feeding, ask a health care professional before use.

Keep out of reach of children. In case of overdose, get medical help or contact a Poison Control Center right away.

Do not use if tamper evident seal is broken or missing.

Store in a cool, dry place.

KEEP OUT OF REACH OF CHILDREN:

In case of overdose, get medical help or contact a Poison Control Center right away.

DIRECTIONS:

• 10 drops orally, 3 times a day.

Consult a health care professional for use in children under 12 years of age.

INACTIVE INGREDIENTS:

Demineralized Water, 25% Ethanol

QUESTIONS:

Distributed by:

BioActive Nutritional, Inc.

1803 N. Wickham Rd.

Melbourne, FL 32935

bioactivenutritional.com

1-800-288-9525

PACKAGE DISPLAY LABEL:

BIOActive Nutritional
OVAPLEX

HOMEOPATHIC
1 FL OZ (30 mL)